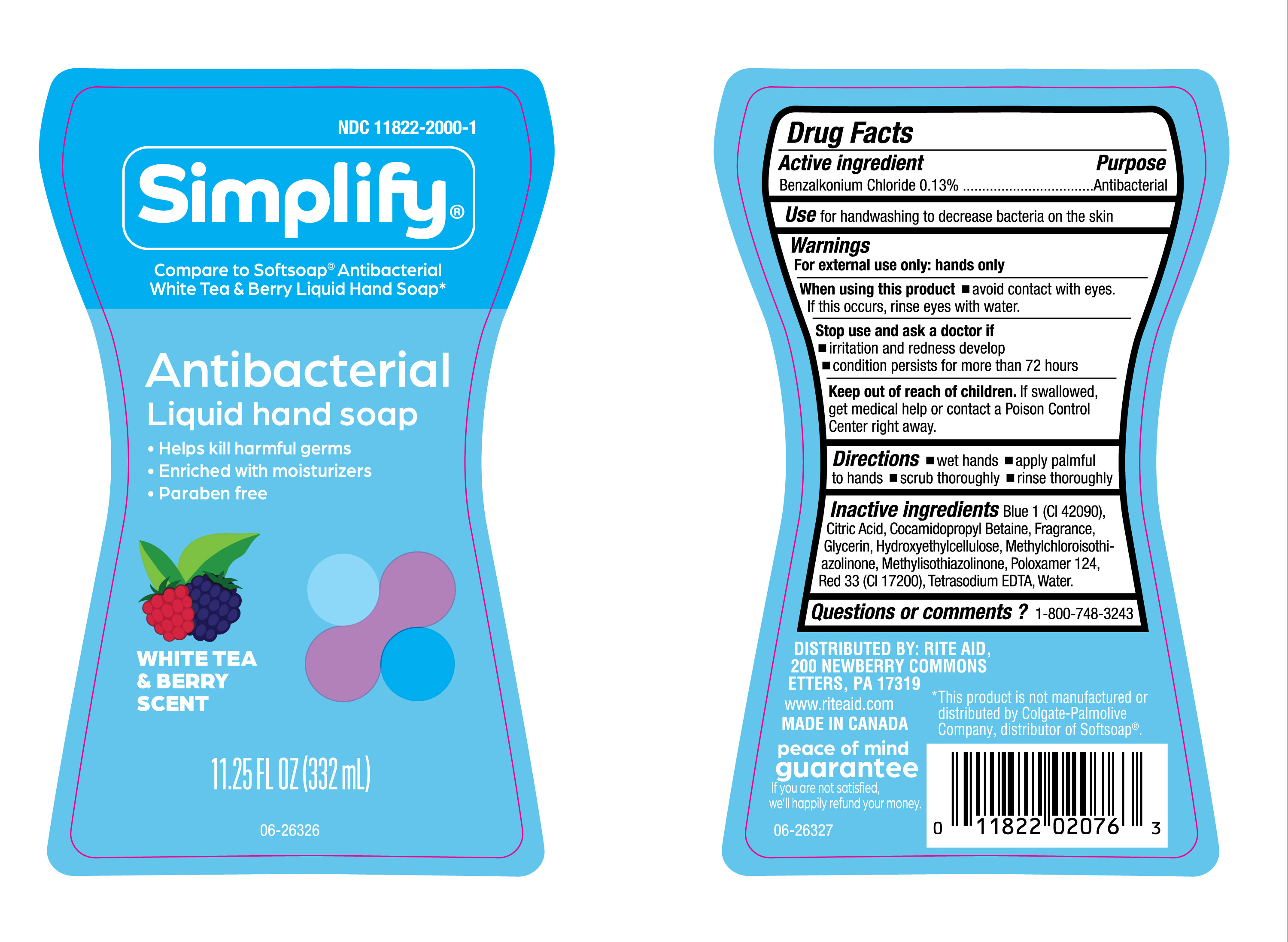 DRUG LABEL: Simplify White Tea LHS
NDC: 11822-2000 | Form: LIQUID
Manufacturer: RITE AID CORPORATION
Category: otc | Type: HUMAN OTC DRUG LABEL
Date: 20250116

ACTIVE INGREDIENTS: BENZALKONIUM CHLORIDE 130 mg/100 mL
INACTIVE INGREDIENTS: METHYLCHLOROISOTHIAZOLINONE; BLUE 1; GLYCERIN; TETRASODIUM EDTA; METHYLISOTHIAZOLINONE; CITRIC ACID; FRAGRANCE CLEAN ORC0600327; HYDROXYETHYLCELLULOSE; COCAMIDOPROPYL BETAINE; POLOXAMER 124; RED 33

NDC- 11822-2000, Simplify White Tea and Berry Liquid Hand Soap.

Active Ingredient

Benzalkonium Chloride 0.13%

Purpose

Antibacterial

Use

For Handwashing to decrease bacteria on the skin.

Warnings

For externaluse only: hands only.

When using the product

- Avoid contact with eyes. If this occurs, rinse eyes with water.

Stop use and ask a doctor if

- irritation and redness develop.
- condition persists for more than 72 hours.

Keep out of reach of children.

If swallowed, get mdical help or contact a Poison Control Center right away.

Directions

- Wet Hands,
- Apply palmful to hands.
- Scrub thoroughly.
- rinse thoroughly.

Inactive Ingredients

Blue 1 (CI 42090), Citric Acid, Cocamidopropyl Betaine, Fragrance, Glycerin, Hydroxyethylcellulose, Methylchloroisothiazolinone, Methylisothiazolinone, Poloxamer 124, Red 33 (CI 17200), Tetrasodium EDTA, Water.

Questions or comments?

1-800-748-3243